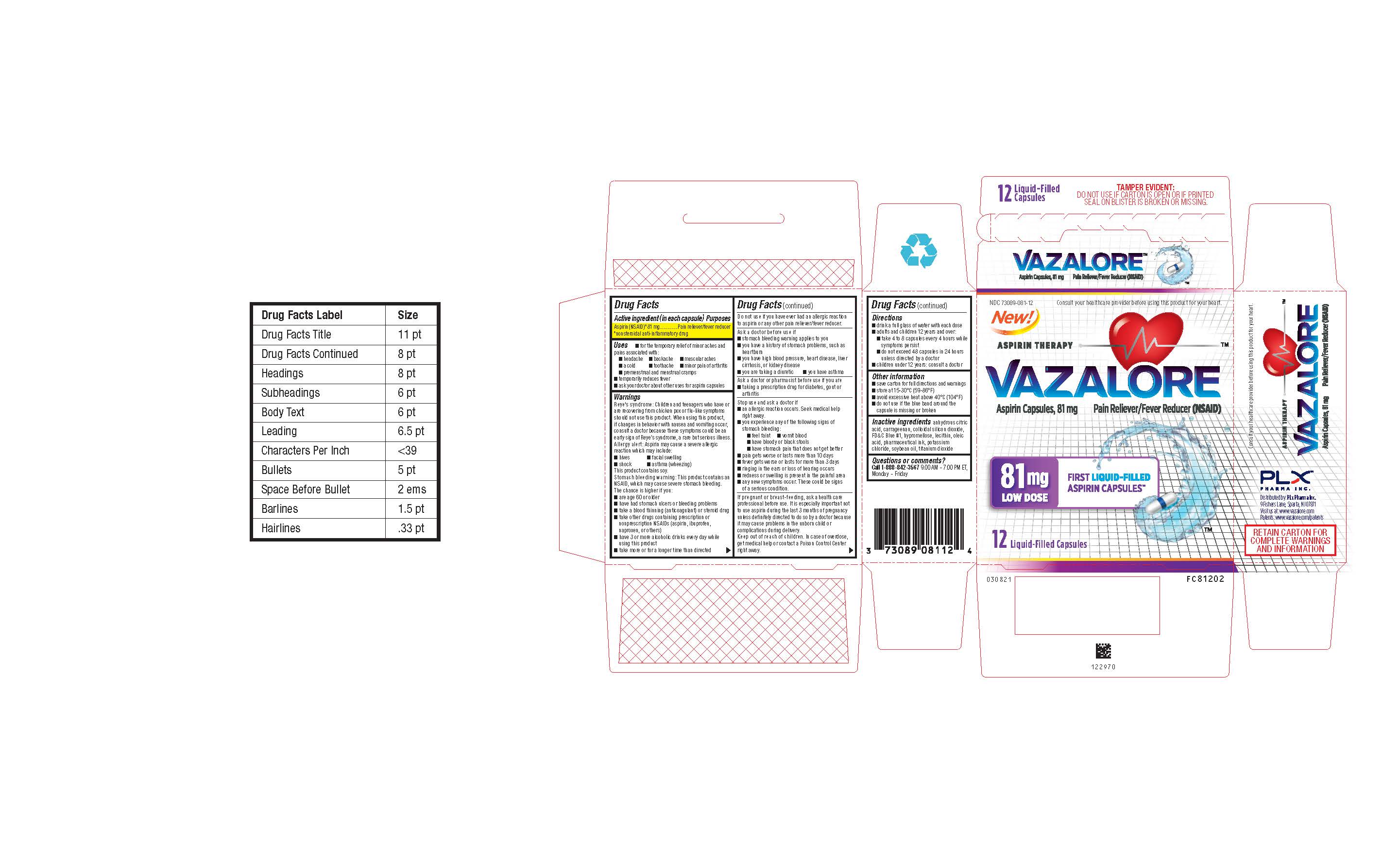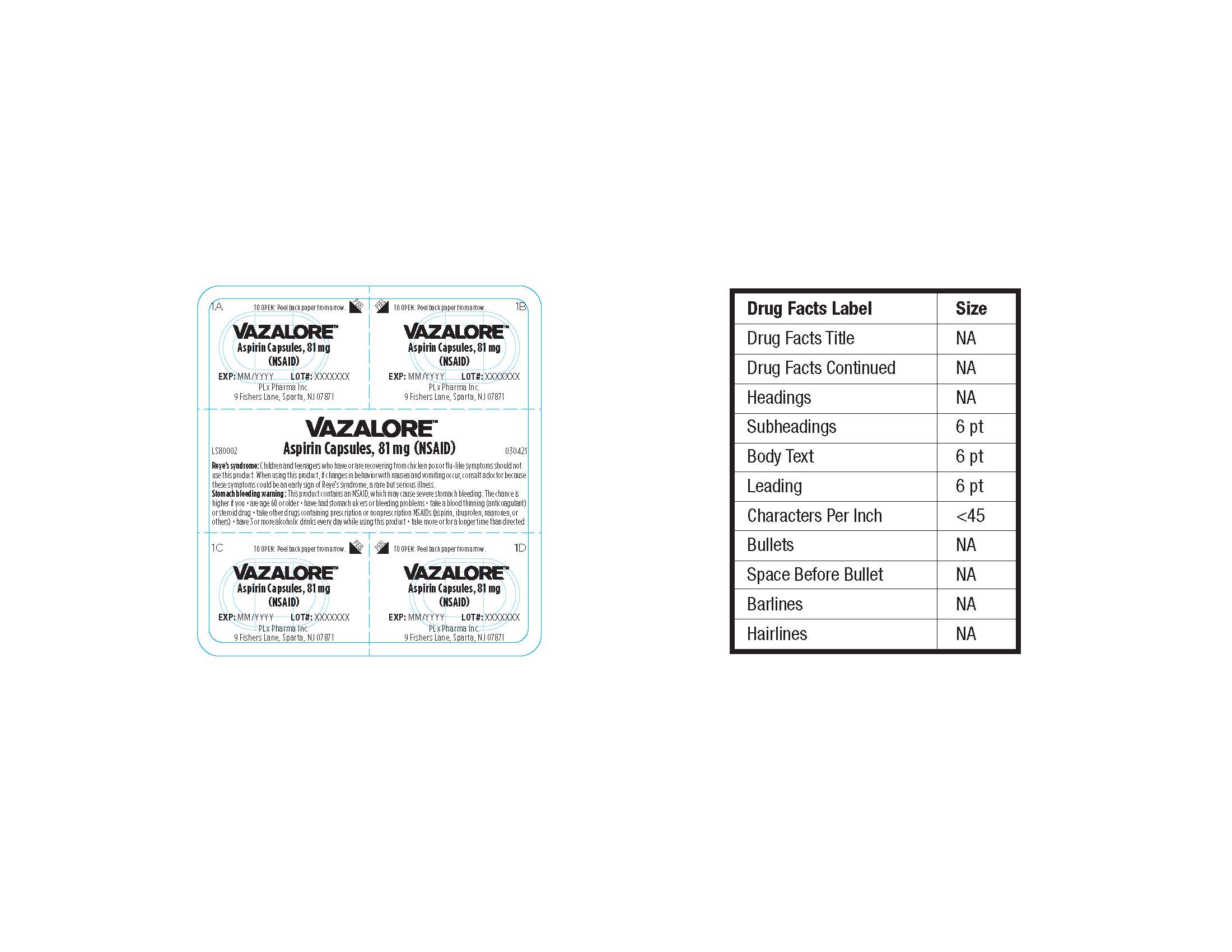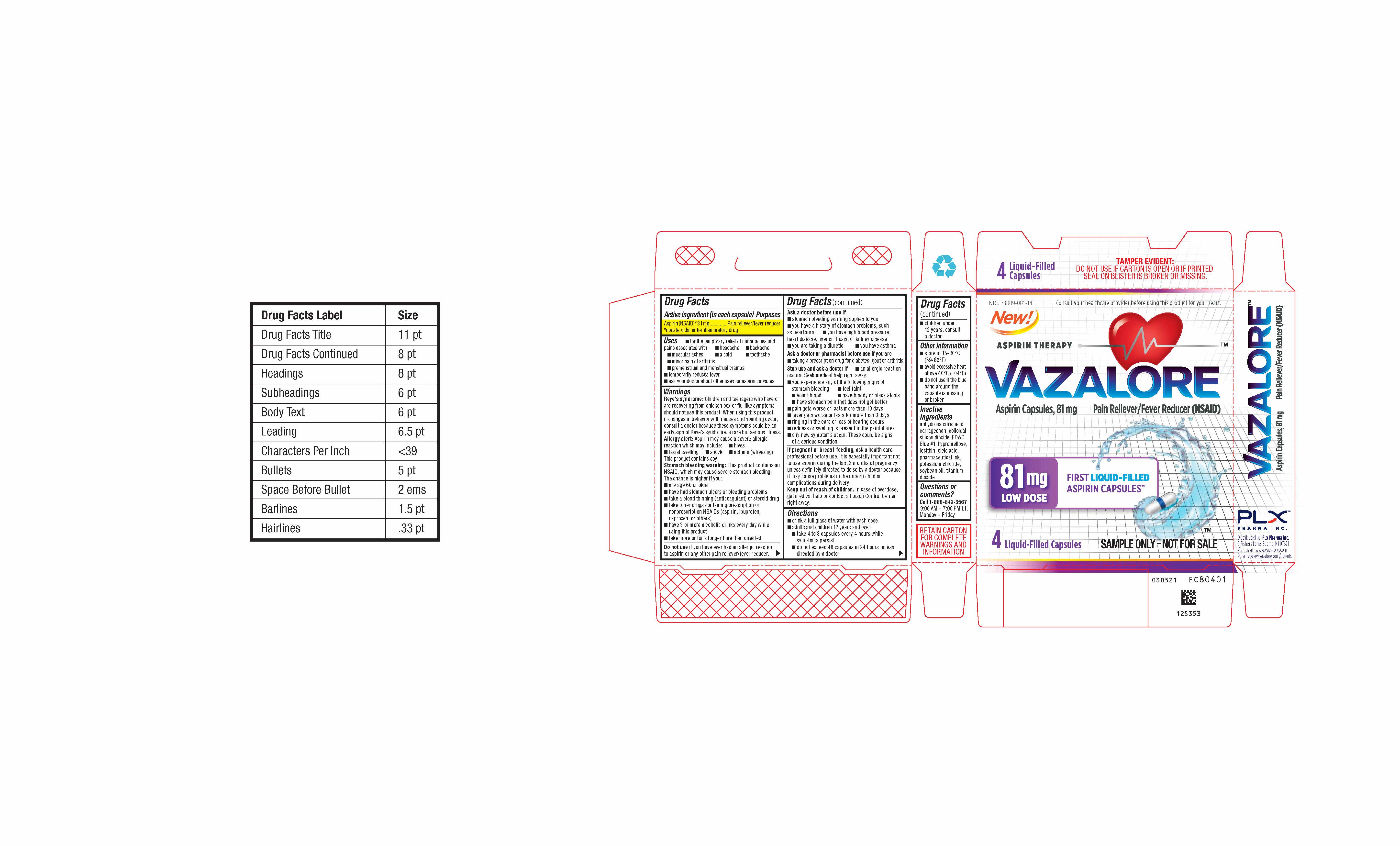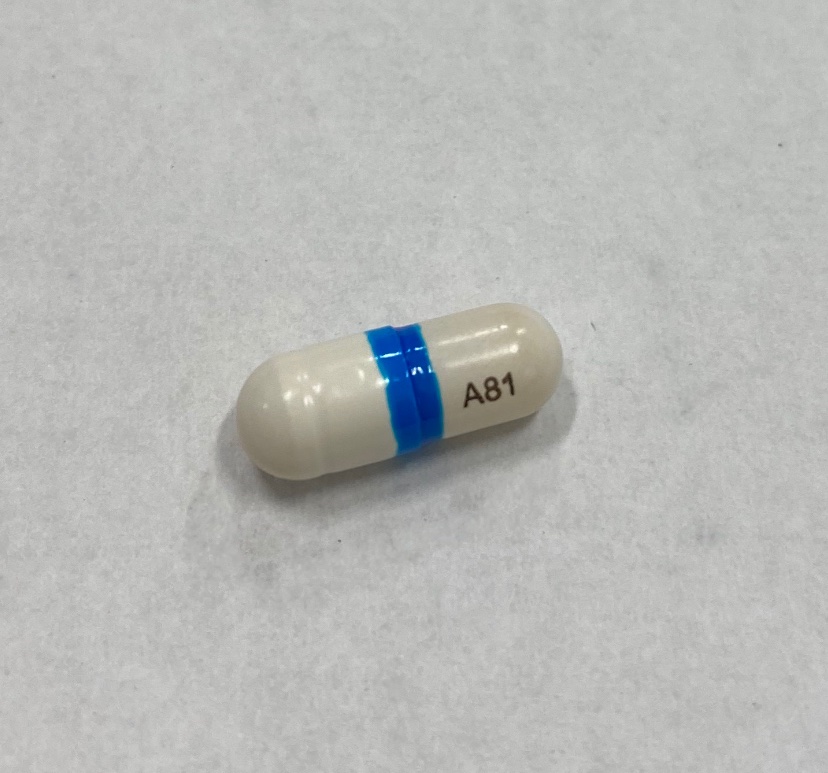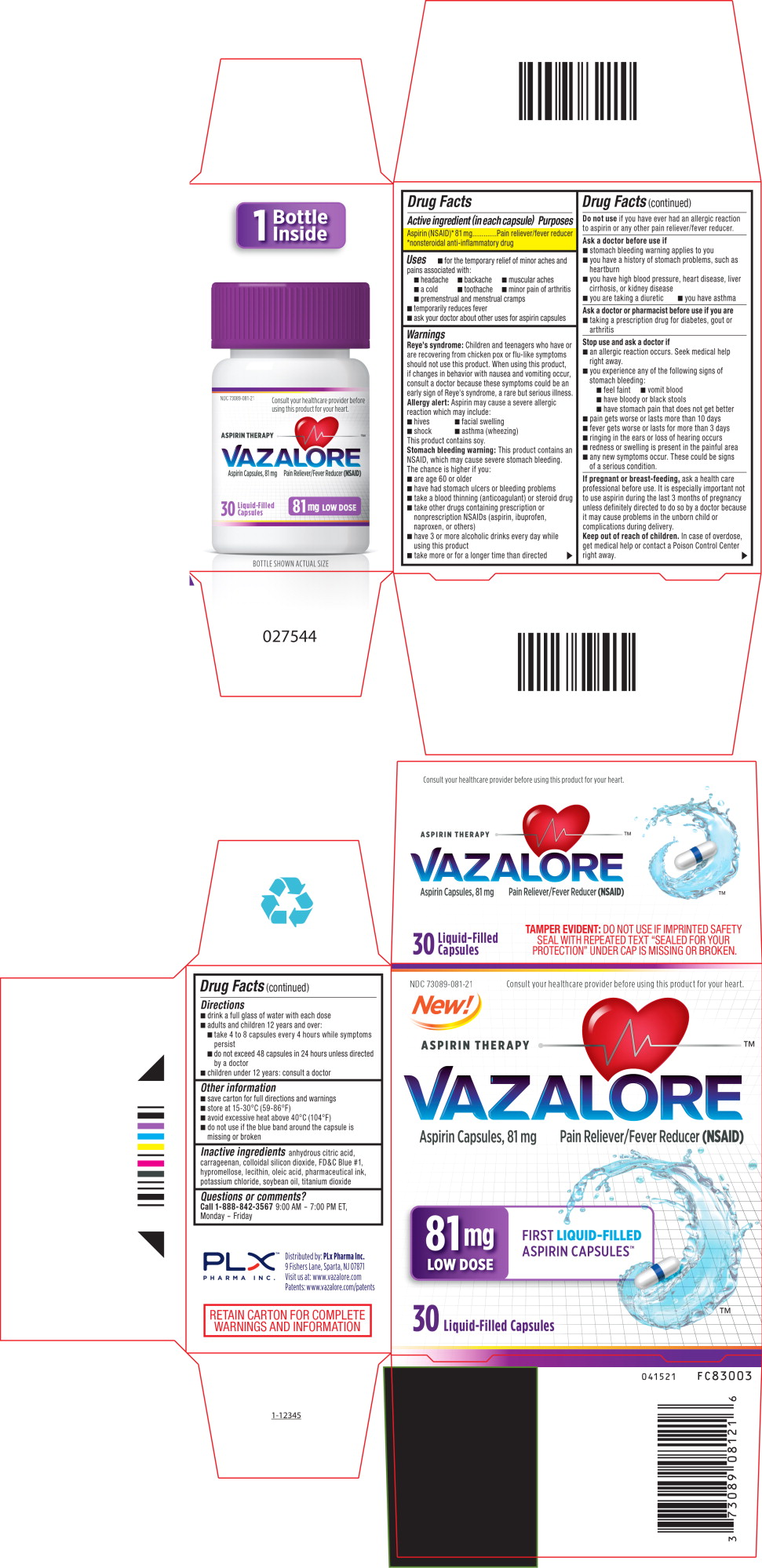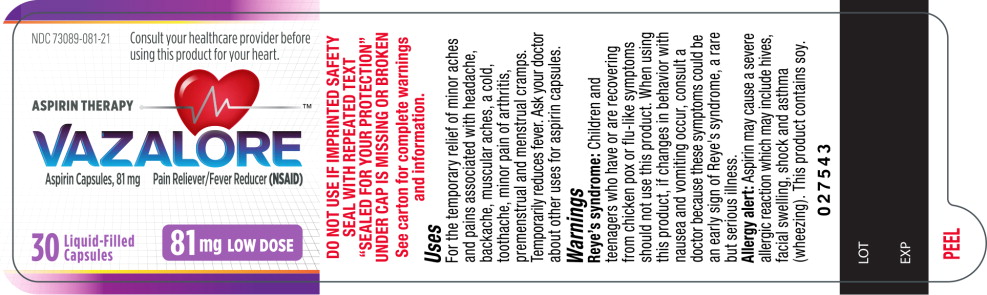 DRUG LABEL: VAZALORE
NDC: 73089-081 | Form: CAPSULE
Manufacturer: PLx Pharma Inc
Category: otc | Type: HUMAN OTC DRUG LABEL
Date: 20241230

ACTIVE INGREDIENTS: ASPIRIN 81 mg/81 mg
INACTIVE INGREDIENTS: ANHYDROUS CITRIC ACID; CARRAGEENAN; SILICON DIOXIDE; OLEIC ACID; POTASSIUM CHLORIDE; SOYBEAN OIL; FD&C BLUE NO. 1; HYPROMELLOSE, UNSPECIFIED; LECITHIN, SOYBEAN; TITANIUM DIOXIDE

VAZALORE (aspirin) Capsules

Uses

- For temporary relief of minor aches and pains associated with:
- headache
- Backache
- muscular aches
- a cold
- toothache
- minor pains of arthritis
- premenstrual and menstrual cramps
- temporarily redices fever
- n ask your doctor about other uses of aspirin capsules

Warnings

Reye’s Syndrome: Children and teenagers who have or are recovering from chicken pox or flu-like symptoms should not use this product. When using this product, if changes in behavior with nausea and vomiting occur, consult a doctor because these symptoms could be an early sign of Reye’s syndrome, a rare but serious illness.

Allergy Alert: Aspirin may cause a severe allergic reaction which may include

n hives n facial wseelling n shock n astham (wheezing)

This product contains soy

Stomach bleeding warning: This product contains an NSAID, which may cause bleeding. The chance is higher if you:

- Are age 60 or older
- Have had stomach ulcers or bleeding problems
- Take a blood thinning (anticoagulant) or steroid drug
- Take other drugs containing prescription or nonprescription NSAIDs (aspirin, ibuprofen, naproxen, or others)
- Have 3 or more alcoholic drinks every day while using this product
- Take more or for a longer time than directed

Active Ingredient (in Each capsules)

Aspirin (NSAID)* 325mg

*Non steroidal Anti inflammatory Drug

Ask a doctor before use if:

- Stomach bleeding warning applies to you
- You have a history of stomach problems, such as heartburn
- You have high blood pressure, heart disease, liver cirrhosis, or kidney disease
- You are taking a diuretic
- You have asthma

Do not use If you have ever had an allergic reaction to aspirin or any other pain reliever / fever reducer

Ask a doctor or a pharmacist before you use if you are

- Taking a drug for diabetes, gout or arthritis

Stop use and ask a doctor if

- An allergic reaction occurs. Seek medical help right away
- You experience amu of the following signs of stomach bleeding

- Feel faint - vomit blood - have bloody or black stool - have stomach pain that does not get better

- Pain gets worse or lasts more than 10 days
- Fever gets worse or lasts more than 3 days
- Ringing in the ears or loss of hearing occurs
- Redness and swelling is present in the painful area
- Any new symptoms occur. These could be signs of serious conditions

Keep out of reach of children. In case of overdose, get medical help or contact a Poison Control Center right away

PREGNANCY OR BREAST FEEDING

If pregnant or breast feeding, ask a healthcare professional before use. It is especially important not to use aspirin during the last 3 months of pregnancy unless definitely directed to do so by a doctor because it may cause problems in the unborn child or complications during delivery

Purposes:

Aspirin (NSAID)* 325mg __ Pain reliever / fever reducer

*Non steroidal Anti inflammatory Drug

Questions or Comments

Call 1-888-842-3569 9:00 AM – 7:00 PM ET, Monday – Friday

RETAIN CARTON FOR COMPLETE WARNINGS AND INFORMATION

Other Information

- Save carton for full directions and warnings
- Store at 15-30°C (59-86°F)
- Avoid excessive heat above 40°C (104°F)
- Do not use if the blue band around the capsule is missing or broken

Inactive ingredients

Anhydrous citric acid, carrageenan, colloidal silicon dioxide, FD&C blue #1, Hypromellose, lecithin, oleic acid, pharmaceutical ink, potassium chloride, soybean oil, titanium dioxide

Directions

- Drink a full glass of water with each dose
- Adults and children 12 years and over:
  - Take 1 or 2 capsules every 4 hours or 3 capsules every 6 hours while symptoms persist
  - Do not exceed 12 capsules in 24 hours
- Children under 12 years consult a doctor